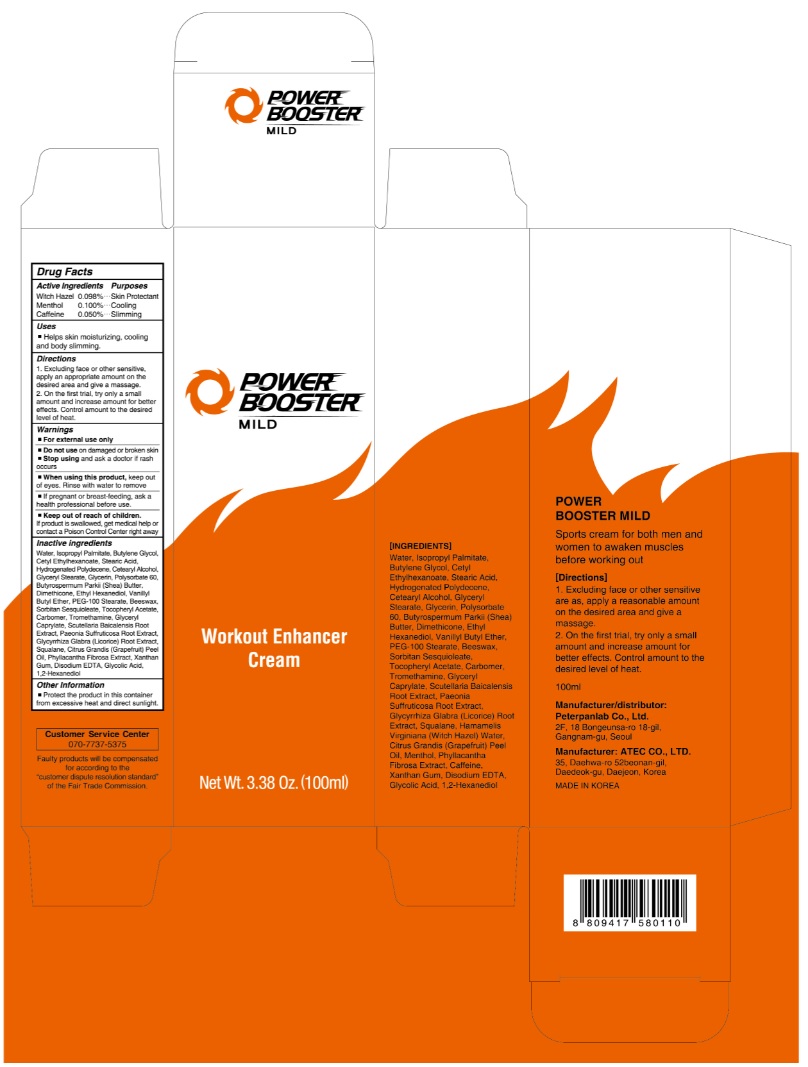 DRUG LABEL: Powerbooster Mild
NDC: 70843-002 | Form: CREAM
Manufacturer: Peterpanlab
Category: otc | Type: HUMAN OTC DRUG LABEL
Date: 20180726

ACTIVE INGREDIENTS: WITCH HAZEL 0.098 g/100 mL; MENTHOL 0.1 g/100 mL; CAFFEINE 0.05 g/100 mL
INACTIVE INGREDIENTS: WATER; ISOPROPYL PALMITATE; BUTYLENE GLYCOL; CETYL ETHYLHEXANOATE; STEARIC ACID; HYDROGENATED POLYDECENE (550 MW); CETOSTEARYL ALCOHOL; GLYCERYL MONOSTEARATE; GLYCERIN; POLYSORBATE 60; SHEA BUTTER; DIMETHICONE; VANILLYL BUTYL ETHER; ETHOHEXADIOL; PEG-100 STEARATE; YELLOW WAX; SORBITAN SESQUIOLEATE; .ALPHA.-TOCOPHEROL ACETATE; CARBOXYPOLYMETHYLENE; TROMETHAMINE; GLYCERYL MONOCAPRYLATE; SCUTELLARIA BAICALENSIS ROOT; SQUALANE; GLYCYRRHIZA GLABRA; CITRUS MAXIMA FRUIT RIND OIL; XANTHAN GUM; GLYCOLIC ACID; EDETATE DISODIUM ANHYDROUS; 1,2-HEXANEDIOL

Drug Facts_70843-002 Powerbooster Mild

ACTIVE INGREDIENT

Witch Hazel 0.098%

Menthol 0.1%

Caffeine 0.050%

PURPOSE

Skin Protectant

Cooling

Slimming

INDICATIONS AND USAGE

Helps skin moiturizing, cooling and body slimming

DOSAGE AND ADMINISTRATION

1. Excluding face or other sensitive, apply an appropriate amount on the desired area and give a massage.
2. On the first trial, try only a small amount and increase amount for better effects. Control amount to the desired level of heat.

WARNINGS

For external use only.
Do not use on damaged or broken skin.Stop using and ask a doctor if rash occurs.
When using this product, keep out of eyes. Rinse with water to remove.

If pregnent or breast-feeding, ask a health professional before use.

KEEP OUT OF REACH OF CHILDREN

Keep out of reach of the children. If product is swallowed, get medical help or contact a poison control center right away.

INACTIVE INGREDIENT

Water, Isopropyl Palmitate, Butylene Glycol, Cetyl Ethylhexanoate, Stearic Acid, Hydrogenated Polydecene, Cetearyl Alcohol, Glyceryl Stearate, Glycerin, Polysorbate 60, Butyrospermum Parkii (Shea) Butter, Dimethicone, Ethyl Hexanediol, Vanillyl Butyl Ether, PEG-100 Stearate, Beeswax, Sorbitan Sesquioleate, Tocopheryl Acetate, Carbomer, Tromethamine, Glyceryl Caprylate, Scutellaria Baicalensis Root Extract, Paeonia Suffruticosa Root Extract, Glycyrrhiza Glabra (Licorice) Root Extract, , Squalane, Citrus Grandis (Grapefruit) Peel Oil, Phyllacantha Fibrosa Extract, Xanthan Gum, Disodium EDTA, Glycolic Acid, 1,2-Hexanediol